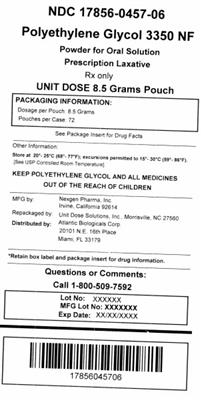 DRUG LABEL: Polyethylene Glycol 3350
NDC: 17856-0457 | Form: POWDER, FOR SOLUTION
Manufacturer: Atlantic Biologicals Corps
Category: prescription | Type: HUMAN PRESCRIPTION DRUG LABEL
Date: 20180522

ACTIVE INGREDIENTS: POLYETHYLENE GLYCOL 3350 17 g/17 g

Polyethylene Glycol 3350 NF
Polyethylene Glycol 3350 Powder for
Oral Solution

DESCRIPTION

A white powder for reconstitution. Polyethylene Glycol 3350 NF (Polyethylene Glycol 3350 Powder For Oral Solution) is a synthetic polyglycol having an average molecular weight of 3350. The actual molecular weight is not less than 90.0 percent and not greater than 110.0 percent of the nominal value. The chemical formula is HO(C2H4O)nH in which n represents the average number of oxyethylene groups. Below 55°C it is a free flowing white powder freely soluble in water. Polyethylene Glycol 3350 NF is an osmotic agent for the treatment of constipation.

CLINICAL PHARMACOLOGY

Pharmacology

Polyethylene Glycol 3350 NF is an osmotic agent which causes water to be retained with the stool. Essentially, complete recovery of Polyethylene Glycol 3350 NF was shown in normal subjects without constipation. Attempts at recovery of Polyethylene Glycol 3350 NF in constipated patients resulted in incomplete and highly variable recovery. In vitro study showed indirectly that Polyethylene Glycol 3350 NF was not fermented into hydrogen or methane by the colonic microflora in human feces. Polyethylene Glycol 3350 NF appears to have no effect on the active absorption or secretion of glucose or electrolytes. There is no evidence of tachyphylaxis.

CLINICAL TRIALS

In one study, patients with less than 3 bowel movements per week were randomized to Polyethylene Glycol 3350 NF, 17 grams, or placebo for 14 days. An increase in bowel movement frequency was observed for both treatment groups during the first week of treatment. Polyethylene Glycol 3350 NF was statistically superior to placebo during the second week of treatment. In another study, patients with 3 bowel movements or less per week and/or less than 300 grams of stool per week were randomized to 2 dose levels of Polyethylene Glycol 3350 NF or placebo for 10 days each. Success was defined by an increase in both bowel movement frequency and daily stool weight. For both parameters, superiority of the 17 gram dose of Polyethylene Glycol 3350 NF over placebo was demonstrated.

INDICATIONS AND USAGE

For the treatment of occasional constipation. This product should be used for 2 weeks or less or as directed by a physician.

CONTRAINDICATIONS

Polyethylene Glycol 3350 NF is contraindicated in patients with known or suspected bowel obstruction and patients known to be allergic to polyethylene glycol.

WARNINGS

Patients with symptoms suggestive of bowel obstruction (nausea, vomiting, abdominal pain or distention) should be evaluated to rule out this condition before initiating Polyethylene Glycol 3350 NF therapy.

PRECAUTIONS

General

Patients presenting with complaints of constipation should have a thorough medical history and physical examination to detect associated metabolic, endocrine and neurogenic conditions and medications. A diagnostic evaluation should include a structural examination of the colon. Patients should be educated about good defecatory and eating habits (such as high fiber diets) and lifestyle changes (adequate dietary fiber and fluid intake, regular exercise) which may produce more regular bowel habits.

Polyethylene Glycol 3350 NF should be administered after being dissolved in approximately 4 to 8 ounces of water, juice, soda, coffee or tea.

Information for Patients

Polyethylene Glycol 3350 NF softens the stool and increases the frequency of bowel movements by retaining water in the stool. It should always be taken by mouth after being dissolved in 4 to 8 ounces of water, juice, soda, coffee, or tea. Should unusual cramps, bloating, or diarrhea occur, consult your physician.

Two to 4 days may be required to produce a bowel movement. This product should be used for 2 weeks or less or as directed by your physician. Prolonged, frequent or excessive use of Polyethylene Glycol 3350 NF may result in electrolyte imbalance and dependence on laxatives.

Laboratory Tests

No clinically significant effects on laboratory tests have been demonstrated.

Drug Interactions

No specific drug interactions have been demonstrated.

Carcinogenesis, Mutagenesis, Impairment of Fertility

Long term carcinogenicity studies, genetic toxicity studies or reproductive toxicity studies in animals have not been performed with Polyethylene Glycol 3350 NF.

Pregnancy

Category C

Animal reproductive studies have not been performed with Polyethylene Glycol 3350 NF.

It is also not known whether Polyethylene Glycol 3350 NF can cause fetal harm when administered to a pregnant woman, or can affect reproductive capacity. Polyethylene Glycol 3350 NF should only be administered to a pregnant woman if clearly needed.

Pediatric Use

Safety and effectiveness in pediatric patients has not been established.

Geriatric Use

There is no evidence for special considerations when Polyethylene Glycol 3350 NF is administered to elderly patients. In geriatric nursing home patients a higher incidence of diarrhea occurred at the recommended 17 g dose. If diarrhea occurs Polyethylene Glycol 3350 NF should be discontinued.

ADVERSE REACTIONS

Nausea, abdominal bloating, cramping and flatulence may occur. High doses may produce diarrhea and excessive stool frequency, particularly in elderly nursing home patients. Patients taking other medications containing polyethylene glycol have occasionally developed urticaria suggestive of an allergic reaction.

OVERDOSAGE

There have been no reports of accidental overdosage. In the event of overdosage, diarrhea would be the expected major event. If an overdose of drug occurred without concomitant ingestion of fluid, dehydration due to diarrhea may result. Medication should be terminated and free water administered. The oral LD50 is > 50 gm/kg in mice, rats and rabbits.

DOSAGE AND ADMINISTRATION

The usual dose is 17 grams (about 1 heaping tablespoon) of powder per day (or as directed by physician) in 4 to 8 ounces of water, juice, soda, coffee, or tea. Each bottle of Polyethylene Glycol 3350 NF is supplied with a dosing cup marked to contain 17 grams of laxative powder when filled to the indicated line. Two to 4 days (48 to 96 hours) may be required to produce a bowel movement.

HOW SUPPLIED

Product: 17856-0457

NDC: 17856-0457-1 17 g in a CUP / 72 in a CASE

NDC: 17856-0457-2 17 g in a POUCH / 72 in a CASE

NDC: 17856-0457-3 4 g in a POUCH / 72 in a CASE

NDC: 17856-0457-4 4.25 g in a POUCH / 72 in a CASE

NDC: 17856-0457-5 8.5 g in a CUP / 72 in a CASE

NDC: 17856-0457-6 8.5 g in a POUCH / 72 in a CASE

Distributed by:
Breckenridge Pharmaceutical, Inc.
Boca Raton, FL 33487

Manufactured by:
Nexgen Pharma, Inc.
Irvine, CA 92614

6920, 6921 Rev 11/08

PATIENT INFORMATION

Polyethylene Glycol 3350 NF (Polyethylene Glycol 3350 Powder for Oral Solution) is a prescription only laxative which has been prescribed by your physician to treat constipation. This product should only be used by the person for whom it was prescribed.

How to take

The dose is 17 grams each day or as directed by physician. It should always be taken by mouth. Measure the dose using the dosing cup (or use one heaping tablespoon of powder), stir and dissolve in a glass (4 to 8 oz) of water, juice, soda, coffee, or tea. Taking more than the prescribed dose may cause loss of fluid due to severe diarrhea.

How will it work

Polyethylene Glycol 3350 NF softens the stool and increases the frequency of bowel movements by retaining water in the stool. Your first bowel movement will usually happen in two to four days, although results may vary for individual patients.

How long should I take it

Polyethylene Glycol 3350 NF achieves its best results when used between one and two weeks. You may discontinue taking the drug after you had several satisfactory bowel movements. Should unusual cramps, bloating, or diarrhea occur, consult your physician. Polyethylene Glycol 3350 NF is intended for up to a two week course of therapy. You should not use for a longer time unless directed by your physician.

Next Steps

After successfully completing Polyethylene Glycol 3350 NF therapy (usually between one and two weeks), please discuss with your physician lifestyle changes which may produce more regular bowel habits (adequate dietary and fluid intake, regular exercise).

Who should NOT take Polyethylene Glycol 3350 NF

Polyethylene Glycol 3350 NF should not be used by children. It should not be used by pregnant women unless prescribed by a physician.

Side Effects/Drug Reactions

Occasionally, Polyethylene Glycol 3350 NF may cause nausea, stomach fullness, cramping, diarrhea and/or gas. Do not take if you have symptoms such as nausea, vomiting, abdominal pain or distention, which may be due to bowel obstruction. On rare occasions hives and skin rashes have been reported which are suggestive of an allergic reaction. If you get an allergic reaction you should discontinue the medication and call your physician. If you are allergic to polyethylene glycol, do not use this drug.